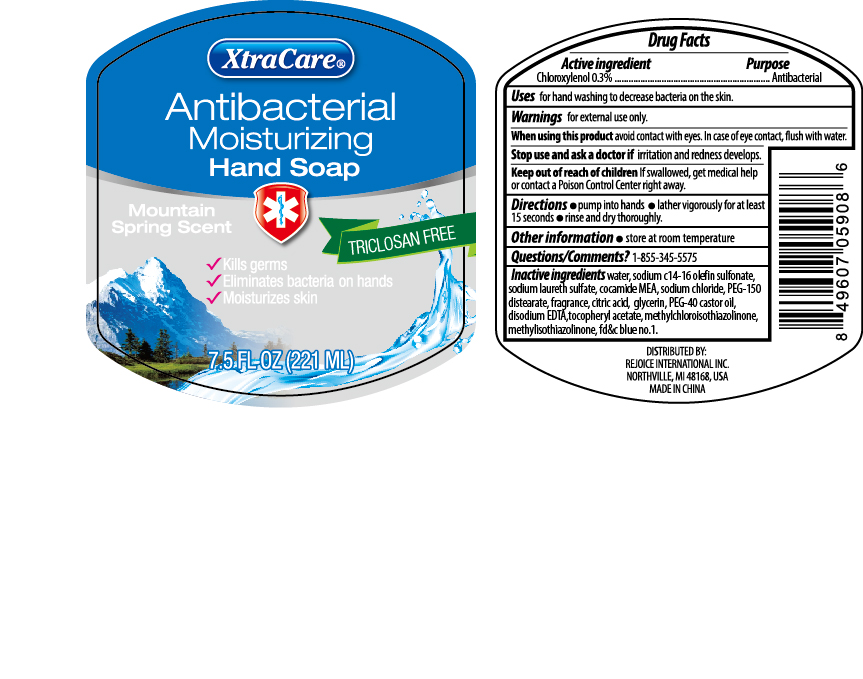 DRUG LABEL: Triclosan Free Antibacterial 7.5 oz (Ocean)
NDC: 57337-088 | Form: LIQUID
Manufacturer: Rejoice International Corp.
Category: otc | Type: HUMAN OTC DRUG LABEL
Date: 20250206

ACTIVE INGREDIENTS: CHLOROXYLENOL 0.3 g/100 mL
INACTIVE INGREDIENTS: WATER; D&C RED NO. 33; GLYCERIN; SODIUM C14-16 OLEFIN SULFONATE; PROPYLENE GLYCOL; SODIUM LAURETH SULFATE; CITRIC ACID MONOHYDRATE; DISODIUM EDTA-COPPER; COCO MONOETHANOLAMIDE; SODIUM CHLORIDE; .ALPHA.-TOCOPHEROL ACETATE; METHYLCHLOROISOTHIAZOLINONE; PEG-150 DISTEARATE; POLYOXYL 40 HYDROGENATED CASTOR OIL; METHYLISOTHIAZOLINONE; FD&C YELLOW NO. 5; FD&C BLUE NO. 1

Triclosan Free Antibacterial 7.5 oz (Ocean)

Purpose

Antibacterial

Active Ingredient

Chloroexylenol, 0.3%

USAGE

For hand washing to decrease bacteria on the skin

Directions

Pump into hands

Lather vigorously for at least 15 seconds

Rinse and dry thoroughly

Keep out of reach of children

If swallowed get medical help or contact a poison control center right away.

Warnings

For external use only

When using this product avoid contact with eyes; in case of eye contact, flush with water

Stop use and ask a doctor if irritation and redness develops

INACTIVE INGREDIENT

WATER, SODIUM LAURETH SULFATE, COCAMIDE MEA, SODIUM C14-16 OLEFIN SULFONATE, SODIUM CHLORIDE, PEG-150 DISTEARATE, FRAGRANCE, CITRIC ACID, GLYCERIN, PEG-40 HYDROGENATED CASTOR OIL, DISODIUM EDTA, TOCOPHERYL ACETATE, METHYLCHLOROTHIAZOLINONE, METHYLISOTHIAZOLINONE, FD&C YELLOW NO.5, D&C RED NO. 33; FD&C BLUE NO. 1